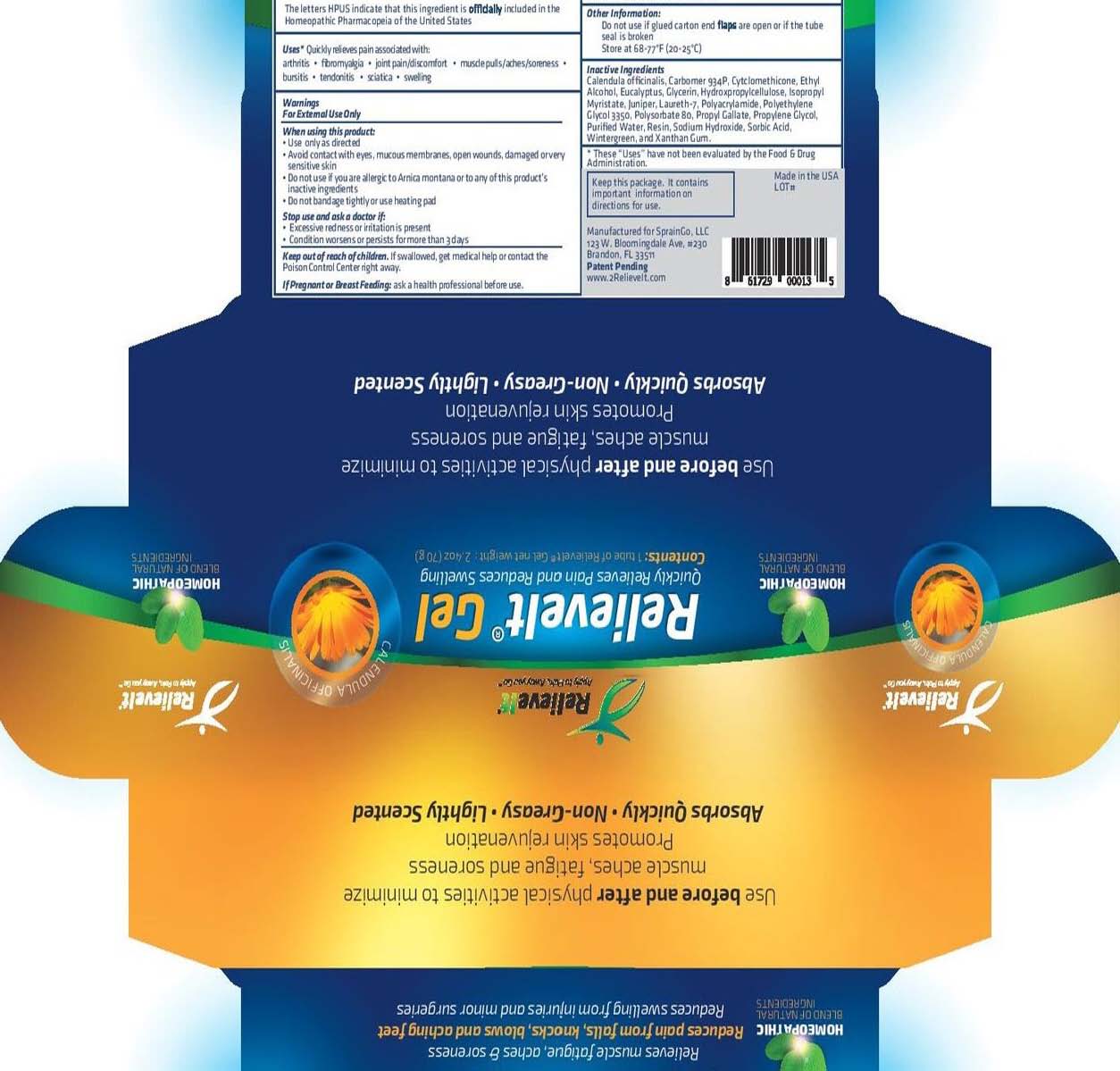 DRUG LABEL: RelieveIt Gel
NDC: 58133-951 | Form: GEL
Manufacturer: Cosmetic Specialty Labs, Inc.
Category: homeopathic | Type: HUMAN OTC DRUG LABEL
Date: 20181113

ACTIVE INGREDIENTS: ARNICA MONTANA 7 [hp_M]/1 g
INACTIVE INGREDIENTS: CYCLOMETHICONE; METHYL ALCOHOL; EUCALYPTUS OIL; LOW-SUBSTITUTED HYDROXYPROPYL CELLULOSE, UNSPECIFIED; JUNIPER BERRY OIL; POLYSORBATE 80; BENZOIN RESIN; SODIUM HYDROXIDE; PROPYLENE GLYCOL 2-METHYLBUTYRATE; POLYETHYLENE GLYCOL 3350; PROPYL GALLATE; CARBOMER 934; GLYCERIN; ISOPROPYL MYRISTATE; POLYACRYLAMIDE (10000 MW); SORBIC ACID; XANTHAN GUM; WATER; AMMONIUM LAURETH-7 SULFATE; GAULTHERIA PROCUMBENS LEAF; CALENDULA OFFICINALIS SEED OIL

RelieveIt Gel

Active Ingredient

Arnica montana 1X HPUS: 7%

Purpose

Arthritis • bursitis • Fibromyalgia • Tendonitis • Joint pain/discomfort

- Sciatica • Swelling • Muscle pulls/aches/soreness

Uses:

Arthritis • Osteoarthritis • Backaches • Bursitis •

Fibromyalgia • Tendonitis • Joint pain/discomfort

• Sciatica • Swelling

Warnings:

for external use only

When using this product:

use only as directed • avoid contact with eyes

or mucous membranes • do not apply to open

wounds, damaged, or very sensitive skin • do

not use if you are allergic to Arnica montana or to any of this product’s

inactive ingredients • do not apply bandage tightly or use heating pad

Keep out of reach of children.

If swallowed, get medical help or contact the

Poison Control Center right away.

Directions:

Adults and children 2 years and over:

•Shake well before using •Apply a sufficient

amount of RelieveIt® Gel to cover the

affected area • Repeat as needed • After

applying, wash hands with soap and water

Children under 2: consult a doctor

Other ingredients:

Calendula officinalis, Carbomer 934P, Cyclomethicone, Ethyl Alcohol,
Eucalyptus, Glycerin, Hydroxypropyl Cellulose,
Isopropyl Myristate, Juniper Oil, Laureth-7, Polyacrylamide, Polyethylene
Glycol 3350, Polysorbate 80, Propyl Gallate,
Propylene Glycol, Purified Water, Resin, Sodium
Hydroxide, Sorbic Acid, Wintergreen, and Xanthan Gum.

*These “Uses” have not been evaluated by the
Food & Drug Administration.

Stop use and ask a doctor if:

excessive redness or irritation is present •

condition worsens • pain persists for more than

3 days

If pregnant or breast feeding:

ask a health professional before use

Other Information

Do not use if glued carton end flaps are open or if tube seal is broken.

Store at 68-77°F (20-25°C)